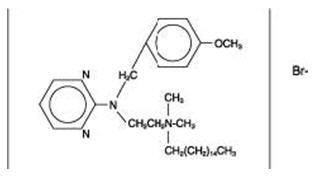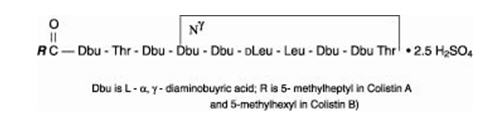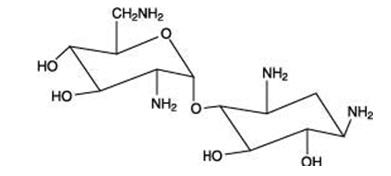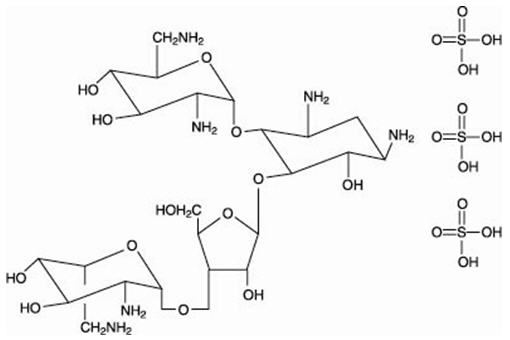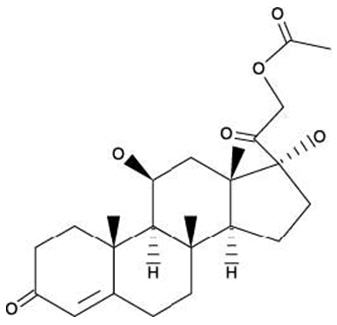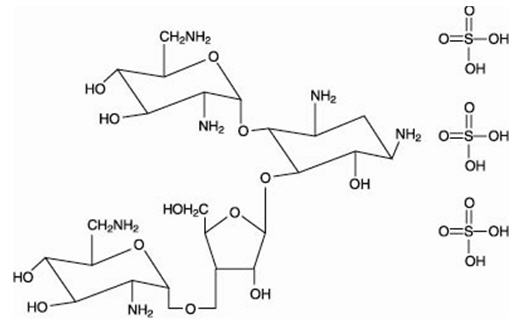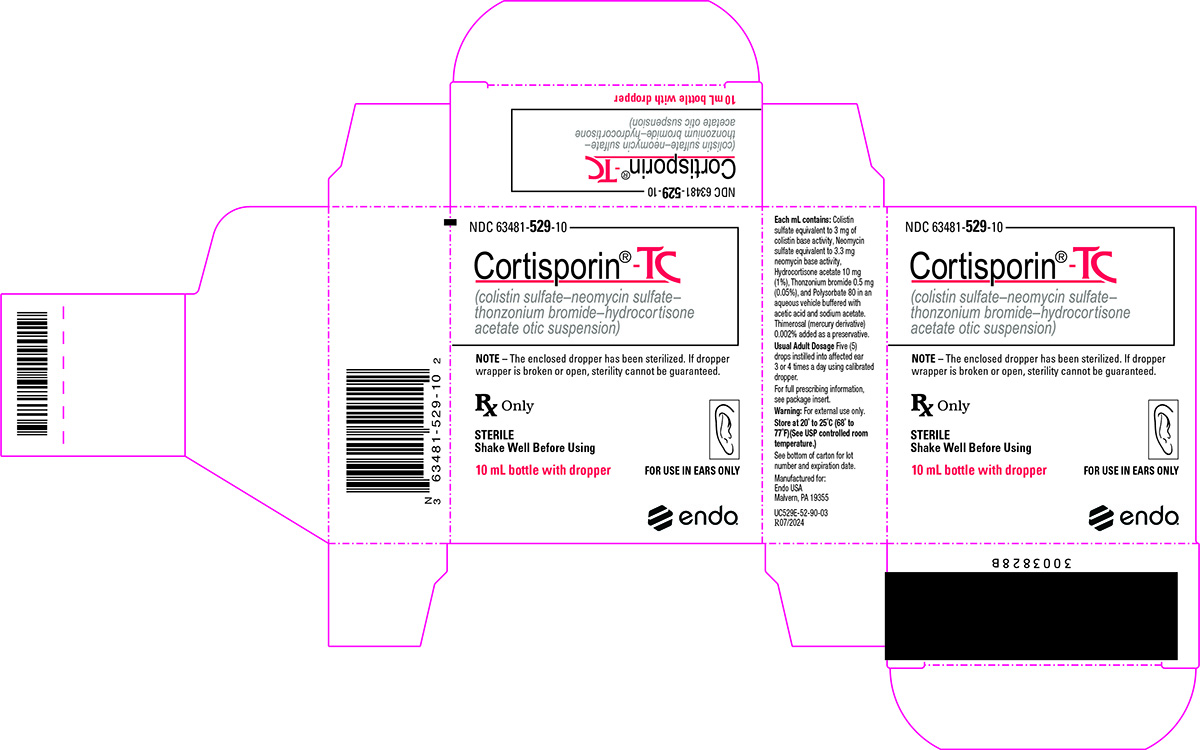 DRUG LABEL: Cortisporin TC
NDC: 63481-529 | Form: SUSPENSION
Manufacturer: Endo USA, Inc.
Category: prescription | Type: HUMAN PRESCRIPTION DRUG LABEL
Date: 20240801

ACTIVE INGREDIENTS: COLISTIN SULFATE 3 mg/1 mL; NEOMYCIN SULFATE 3.3 mg/1 mL; THONZONIUM BROMIDE 0.5 mg/1 mL; HYDROCORTISONE ACETATE 10 mg/1 mL
INACTIVE INGREDIENTS: ACETIC ACID; SODIUM ACETATE; THIMEROSAL; POLYSORBATE 80

Cortisporin®-TC Otic
with Neomycin and Hydrocortisone
(colistin sulfate—neomycin sulfate—thonzonium
bromide—hydrocortisone acetate otic suspension)

DESCRIPTION

Cortisporin® TC Otic with Neomycin and Hydrocortisone (colistin sulfate—neomycin sulfate—thonzonium bromide—hydrocortisone acetate otic suspension) is a sterile antibacterial and anti-inflammatory aqueous suspension containing in each mL: Colistin base activity, 3 mg (as the sulfate); Neomycin base activity, 3.3 mg (as the sulfate); Hydrocortisone acetate, 10 mg (1%); Thonzonium bromide, 0.5 mg (0.05%); Polysorbate 80, acetic acid, and sodium acetate in a buffered aqueous vehicle. Thimerosal (mercury derivative), 0.002%, is added as a preservative. It is a nonviscous liquid, buffered at pH 5, for instillation into the canal of the external ear or direct application to the affected aural skin.

The structural formulas of colistin sulfate (mixture of Colistin A & B), neomycin sulfate (mixture of neomycin A, B & C), hydrocortisone acetate ((11β)-21-(acetyloxy)-11,17-dihydroxypregn) methyl]-2 pyrimidinylamino] ethyl]-N,N-dimethyl-1-hexadecanaminium, bromide) are represented below:

Thonzonium Bromide

Colistin sulfate

Neomycin A

Neomycin B Sulfate

Hydrocortisone Acetate

Neomycin C Sulfate

CLINICAL PHARMACOLOGY

Colistin sulfate is a polypeptide antibiotic which penetrates into and disrupts the bacterial cell membrane. Neomycin sulfate is an aminoglycoside antibiotic which inhibits protein synthesis, disrupting the normal cycle of ribosomal function. Hydrocortisone acetate is a corticosteroid hormone which is thought to act by regulating the rate of protein synthesis; it controls inflammation, edema, pruritus and other dermal reactions. Corticosteroids suppress the inflammatory response to a variety of agents and they may delay healing. Since corticoids may inhibit the body's defense mechanism against infection, a concomitant antimicrobial drug may be used when this inhibition is considered to be clinically significant in a particular case.

The relative potency of corticosteroids depends on the molecular structure, concentration, and release from the vehicle.

Thonzonium bromide is a surface-active agent that promotes tissue contact by dispersion and penetration of the cellular debris and exudate.

Microbiology

Together, colistin sulfate and neomycin sulfate have bactericidal activity against most strains of the following microorganisms, both in vitro and in clinical infections as described in the INDICATIONS AND USAGE section.

Aerobic gram-positive microorganisms:

Staphylococcus aureus.

Aerobic gram-negative microorganisms:

Enterobacter aerogenes

Escherichia coli

Klebsiella pneumoniae

Pseudomonas aeruginosa.

Susceptibility Tests:

It is not recommended that colistin sulfate or neomycin sulfate be routinely tested and reported by clinical microbiology laboratories.

INDICATIONS AND USAGE

Cortisporin® TC Otic is indicated for the treatment of superficial bacterial infections of the external auditory canal, caused by organisms susceptible to the action of the antibiotics; and for the treatment of infections of mastoidectomy and fenestration cavities, caused by organisms susceptible to the antibiotics.

CONTRAINDICATIONS

This product is contraindicated in those individuals who have shown hypersensitivity to any of its components.

This product should not be used if the external auditory canal disorder is suspected or known to be due to cutaneous viral infection (e.g., herpes simplex virus or varicella zoster virus).

WARNINGS

Neomycin can induce permanent sensorineural hearing loss due to cochlear damage, mainly destruction of hair cells in the organ of Corti. The risk is greater with prolonged use. Therapy should be limited to 10 consecutive days (See PRECAUTIONS-General). Patients being treated with eardrops containing neomycin should be under close clinical observation. Cortisporin® TC Otic should be used cautiously in any patient with a perforated tympanic membrane.

Neomycin sulfate may cause cutaneous sensitization. A precise incidence of hypersensitivity reactions (primarily skin rash) due to topical neomycin is not known. Discontinue promptly if sensitivity or irritation occurs.

When using neomycin-containing products to control secondary infection in the chronic dermatoses, such as chronic otitis externa or stasis dermatitis, it should be borne in mind that the skin in these conditions is more liable than is normal skin to become sensitized to many substances, including neomycin. The manifestation of sensitization to neomycin is usually a low-grade reddening with swelling, dry scaling, and itching; it may be manifest simply as a failure to heal. Periodic examination for such signs is advisable, and the patient should be told to discontinue the product if they are observed. These symptoms regress quickly on withdrawing the medication. Neomycin containing applications should be avoided for the patient thereafter.

PRECAUTIONS

General

As with any other antibiotic preparation, prolonged treatment may result in overgrowth of nonsusceptible organisms and fungi. If the infection is not improved after one week, cultures should be repeated to verify the identity of the organism and to determine whether therapy should be changed.

Treatment should not be continued for longer than ten days.

Allergic cross-reactions may occur which could prevent the use of any or all of the aminoglycoside antibiotics for the treatment of future infections.

Information for Patients

Avoid contaminating the dropper with material from the ear, fingers, or other source. This caution is necessary if the sterility of the drops is to be preserved.

If sensitization or irritation occurs, discontinue use immediately and contact your physician.

Do not use in the eyes.

If you prefer to warm the medication before using it, do not heat the suspension above body temperature in order to avoid loss of potency.

SHAKE WELL BEFORE USING.

Laboratory Tests

Systemic effects of excessive levels of hydrocortisone may include a reduction in the number of circulating eosinophils and a decrease in urinary excretion of 17-hydroxycorticosteroids.

Carcinogenesis, Mutagenesis, Impairment of Fertility

Long-term animal carcinogenicity studies have not been performed with colistin or neomycin, or Cortisporin® TC Otic. An increased incidence of chromosome aberrations in human lymphocytes has been reported following in vitro exposure to colistin or neomycin.

Fertility studies have not been performed with neomycin, but reports from the scientific literature suggest that it may decrease spermatogenesis in rats. No adverse effects on fertility were observed in male or female rats given intramuscular doses of colistimethate sodium, the methanesulfonate salt of colistin, up to 20 mg/kg (equivalent to 9.3 mg/kg of colistin base). This is approximately 30 times the clinical daily dose based on body surface area, assuming 100% absorption from the ear; however, significant systemic levels of colistin or neomycin would not be anticipated in humans when Cortisporin® TC Otic is used as directed.

Long term studies in rodents showed no evidence of carcinogenicity attributable to oral administration of corticosteroids. Mutagenicity studies with hydrocortisone were negative. Studies have not been performed to evaluate the effect on fertility of topical corticosteroids.

Pregnancy

Teratogenic Effects

Pregnancy Category C

There are no adequate and well controlled studies of Cortisporin® TC Otic in pregnant women. It is not known whether Cortisporin® TC Otic can cause fetal harm when administered to a pregnant woman.

Colistimethate sodium, the methanesulfonate salt of colistin, was not teratogenic in rats or rabbits given intramuscular doses up to 20 mg/kg (equivalent to 9.3 mg/kg of colisitin base, approximately 30 times (rats) or 55 times (rabbits) the clinical daily dose based on body surface area and assuming 100% absorption from the ear). Increased resorptions were observed in rabbits at 20 mg/kg, but not 10 mg/kg (equivalent to 4.15 mg/kg of colistin base). Decreased pup survival at weaning was observed in rats at 20 mg/kg, a maternally toxic dose of colistin, but not 10 mg/kg. Colistin has not been shown to have any adverse effects on the developing embryo or fetus at doses relevant to the amount that will be delivered ototopically at the recommended clinical doses.

Although aminoglycosides can cause congenital deafness in humans if administered during pregnancy, significant systemic levels of neomycin would not be anticipated when Cortisporin® TC Otic is used as directed.

Corticosteroids are generally teratogenic in laboratory animals when administered systemically at relatively low dosage levels. The more potent corticosteroids have been shown to be teratogenic after dermal application in laboratory animals.

Cortisporin® TC Otic should be used during pregnancy only if the potential benefit justifies the potential risk to the fetus.

Nursing Mothers

Hydrocortisone and colistin sulfate appear in human milk following oral administration of the drugs. Since systemic absorption of these drugs may occur when they are used topically, caution should be exercised when Cortisporin® TC Otic Suspension is used by a nursing woman.

Pediatric Use

See DOSAGE AND ADMINISTRATION.

The safety and effectiveness of Cortisporin® TC Otic in infants below one year of age have not been established. The efficacy of Cortisporin® TC Otic in pediatric patients one year or older in the treatment of superficial bacterial infections of the external auditory canal and for the treatment of infections of mastoidectomy and fenestration cavities has been demonstrated in a controlled clinical trial.

Geriatric Use

No overall differences in safety or effectiveness have been observed between elderly and younger patients.

ADVERSE REACTIONS

Neomycin occasionally causes skin sensitization.

Ototoxicity (see WARNINGS section) and nephrotoxicity have also been reported.

Adverse reactions have occurred with topical use of antibiotic combinations. Exact incidence figures are not available since no denominator of treated patients is available. The reaction occurring most often is allergic sensitization. In one clinical study, using a 20% neomycin patch, neomycin-induced allergic skin reactions occurred in two of 2,175 (0.09%) individuals in the general population. In another study the incidence was found to be approximately 1%.

The following local adverse events have been reported with topical corticosteroids, especially under occlusive dressings: burning, itching, irritation, dryness, folliculitis, hypertrichosis, acneiform eruptions, hypopigmentation, perioral dermatitis, allergic contact dermatitis, maceration of the skin, secondary infection, skin atrophy, striae, and miliaria.

For medical advice about adverse reactions contact your medical professional. To report SUSPECTED ADVERSE REACTIONS, contact Endo at 1-800-462-3636 or FDA at 1-800-FDA-1088 or www.fda.gov/medwatch.

DOSAGE AND ADMINISTRATION

Therapy with this product should be limited to 10 days (See WARNINGS).

The external auditory canal should be thoroughly cleansed and dried with a sterile cotton applicator.

When using the calibrated dropper:

For adults, 5 drops of the suspension should be instilled into the affected ear 3 or 4 times daily. For pediatric patients, 4 drops are suggested because of the smaller capacity of the ear canal.

The patient should lie with the affected ear upward and then the drops should be instilled. This position should be maintained for 5 minutes to facilitate penetration of the drops into the ear canal. Repeat, if necessary, for the opposite ear.

If preferred, a cotton wick may be inserted into the canal and then the cotton may be saturated with the suspension. This wick should be kept moist by adding further solution every 4 hours. The wick should be replaced at least once every 24 hours.

HOW SUPPLIED

Cortisporin® TC Otic is supplied as:

NDC 63481-529-10 10 mL bottle with dropper

Each mL contains: Colistin sulfate equivalent to 3 mg of colistin base activity, Neomycin sulfate equivalent to 3.3 mg neomycin base activity, Hydrocortisone acetate 10 mg (1%), Thonzonium bromide 0.5 mg (0.05%), and Polysorbate 80 in an aqueous vehicle buffered with acetic acid and sodium acetate. Thimerosal (mercury derivative) 0.002% is added as a preservative.

A sterilized dropper-cap assembly for use on the bottle of suspension is included in the package.

Shake well before using.

STORAGE AND HANDLING

Store at 20° to 25°C (68° to 77°F).

Rx only.

Manufactured for:
Endo USA
Malvern, PA 19355

© 2024 Endo, Inc. or one of its affiliates.

Revised: 07/2024